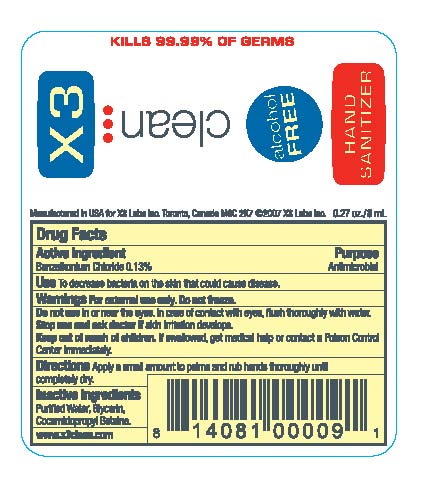 DRUG LABEL: X3 Clean
NDC: 26550-001 | Form: SPRAY
Manufacturer: X3 Labs Inc.
Category: otc | Type: HUMAN OTC DRUG LABEL
Date: 20090824

ACTIVE INGREDIENTS: Benzalkonium Chloride 1.3 uL/1 mL
INACTIVE INGREDIENTS: Water; Glycerin; Cocamidopropyl Betaine 

X3 Hand Sanitizer (Spray)

Purpose Antimicrobial

INDICATIONS AND USAGE

Use To decrease bacteria on the skin that could cause disease.

Warnings For external use only. Do not freeze.
Do not use in or near eyes. In case of contact with eyes, flush thoroughly with water.

Stop use and ask doctor if skin irritation develops.

Keep out of reach of children. If swallowed, get medical help or contact a Poison Control Center immediately.

DOSAGE AND ADMINISTRATION

Directions Apply a small amount to palms and rub hands thoroughly until completely dry.

INACTIVE INGREDIENT

Purified Water, Glycerin, Cocamidopropyl Bentaine.